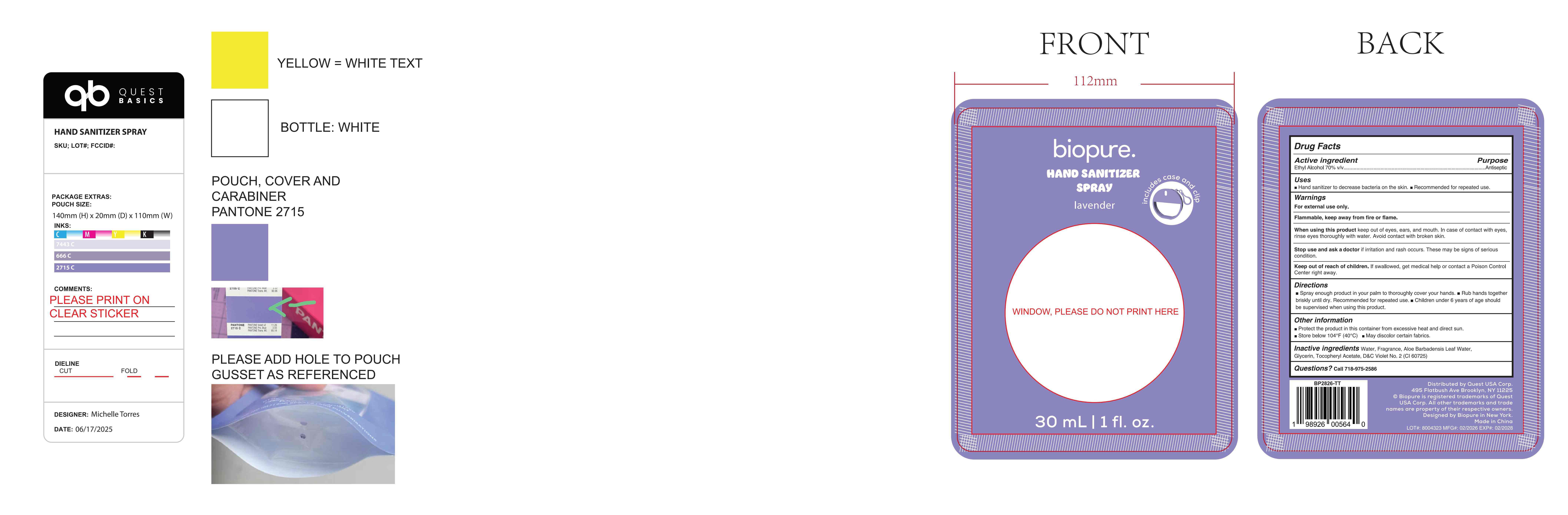 DRUG LABEL: Hand sanitizer
NDC: 87374-001 | Form: SPRAY
Manufacturer: Beimei Biotechnology (Guangzhou) Co., Ltd.
Category: otc | Type: HUMAN OTC DRUG LABEL
Date: 20260126

ACTIVE INGREDIENTS: ALCOHOL 70 mL/100 mL
INACTIVE INGREDIENTS: GLYCERIN; D&C VIOLET NO. 2; FRAGRANCE 13576; WATER; ALOE VERA LEAF OIL; ALPHA-TOCOPHEROL ACETATE

87374-001

Active Ingredient

Ethyl Alcohol 70%

Purpose

Antiseptic

Use

Hand sanitizer to decrease bacteria on the skin, Recommended for repeated use.

Warnings

For external use only
Flammable, keep away from fire or flame

Do not use

if irritation and rash occurs. These may be signs of serious condition.

When Using

When using this product keep out of eye, ears, and mouth. In case of contact with eyes, rinse eyes thoroughly with water. Avoid contact with broken skin

Stop Use

Stop use and ask a doctor if irritation and rash occurs. These may be signs of serious condition.

Ask Doctor

Stop use and ask a doctor if irritation and rash occurs. These may be signs of serious condition.

Keep out of reach of children, if swallowed, get medical help or contact a poison control center right away

Directions

Spray enough product in your palm to thoroughly cover your hands, rub hands together briskly until dry, recommended for repeated use, children under 6 years of age should be supervised when using this product

Other information

Protect the product in this container from excessive heat and direct sun.
Store below 104 °F(40 °C)
May discolor certain fabrics

Inactive ingredients

Water, Fragrance, Aloe Barbadensis Leaf Water, Glycerin, Tocopheryl Acetate, D&C Violet No.2(Cl 60725)

Questions

Call 718-975-2586